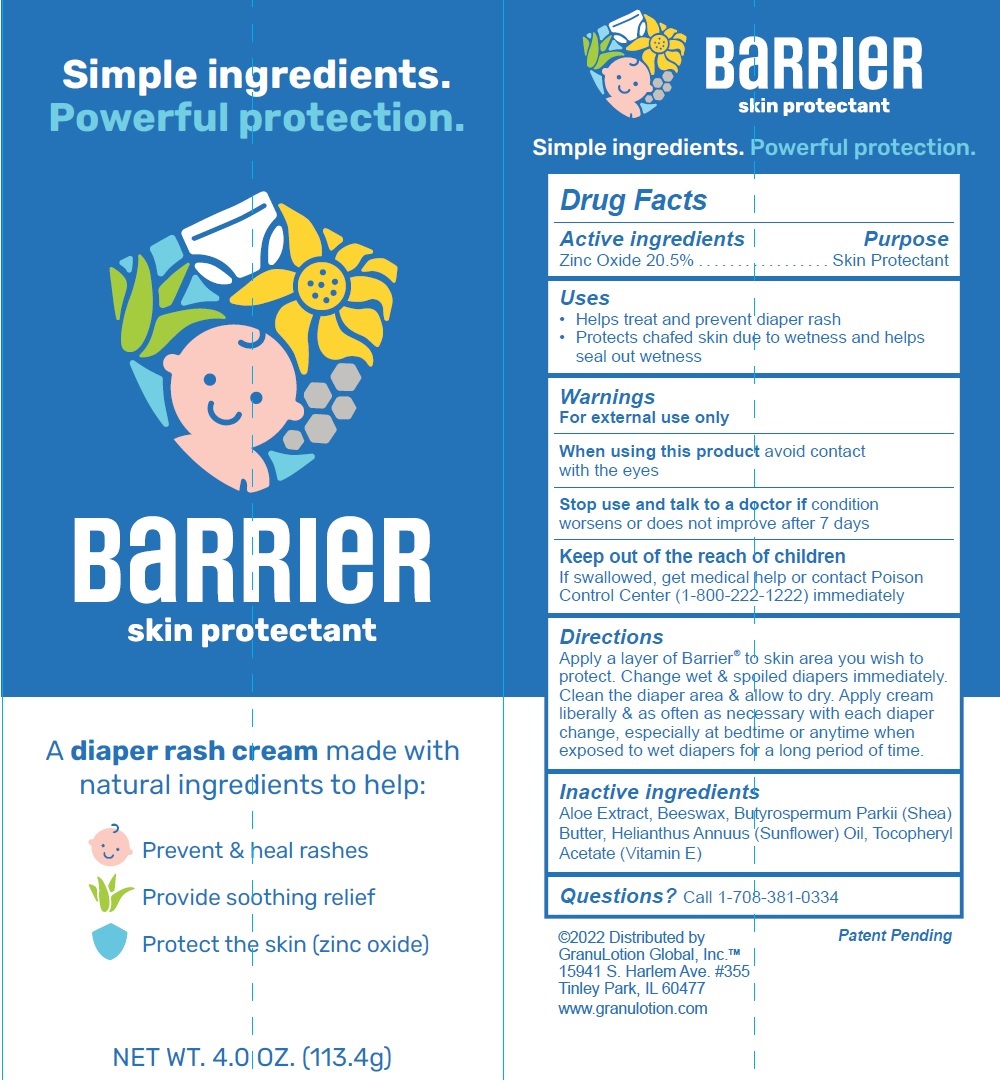 DRUG LABEL: GL HEALTH Barrier Skin Protectant
NDC: 82897-379 | Form: CREAM
Manufacturer: GL HEALTH, INC.
Category: otc | Type: HUMAN OTC DRUG LABEL
Date: 20231106

ACTIVE INGREDIENTS: ZINC OXIDE 205 mg/1 g
INACTIVE INGREDIENTS: ALOE; YELLOW WAX; SHEA BUTTER; HELIANTHUS ANNUUS FLOWERING TOP; .ALPHA.-TOCOPHEROL ACETATE

GL HEALTH Barrier Skin Protectant

Active ingredients

Zinc Oxide 20.5%

Purpose

Skin Protectant

Uses

• Helps treat and prevent diaper rash • Protects chafed skin due to wetness and helps seal out wetness

Warnings

For external use only

When using this product

avoid contact with the eyes

Stop use and talk to a doctor if

condition worsens or does not improve after 7 days

Keep out of the reach of children

If swallowed, get medical help or contact Poison Control Center (1-800-222-1222) immediately

Directions

Apply a layer of Barrier® to skin area you wish to protect. Change wet & spoiled diapers immediately. Clean the diaper area & allow to dry. Apply cream liberally & as often as necessary with each diaper change, especially at bedtime or anytime when exposed to wet diapers for a long period of time.

Inactive ingredients

Aloe Extract, Beeswax, Butyrospermum Parkii (Shea) Butter, Helianthus Annuus (Sunflower) Oil, Tocopheryl Acetate (Vitamin E)

Questions?

Call 1-708-381-0334